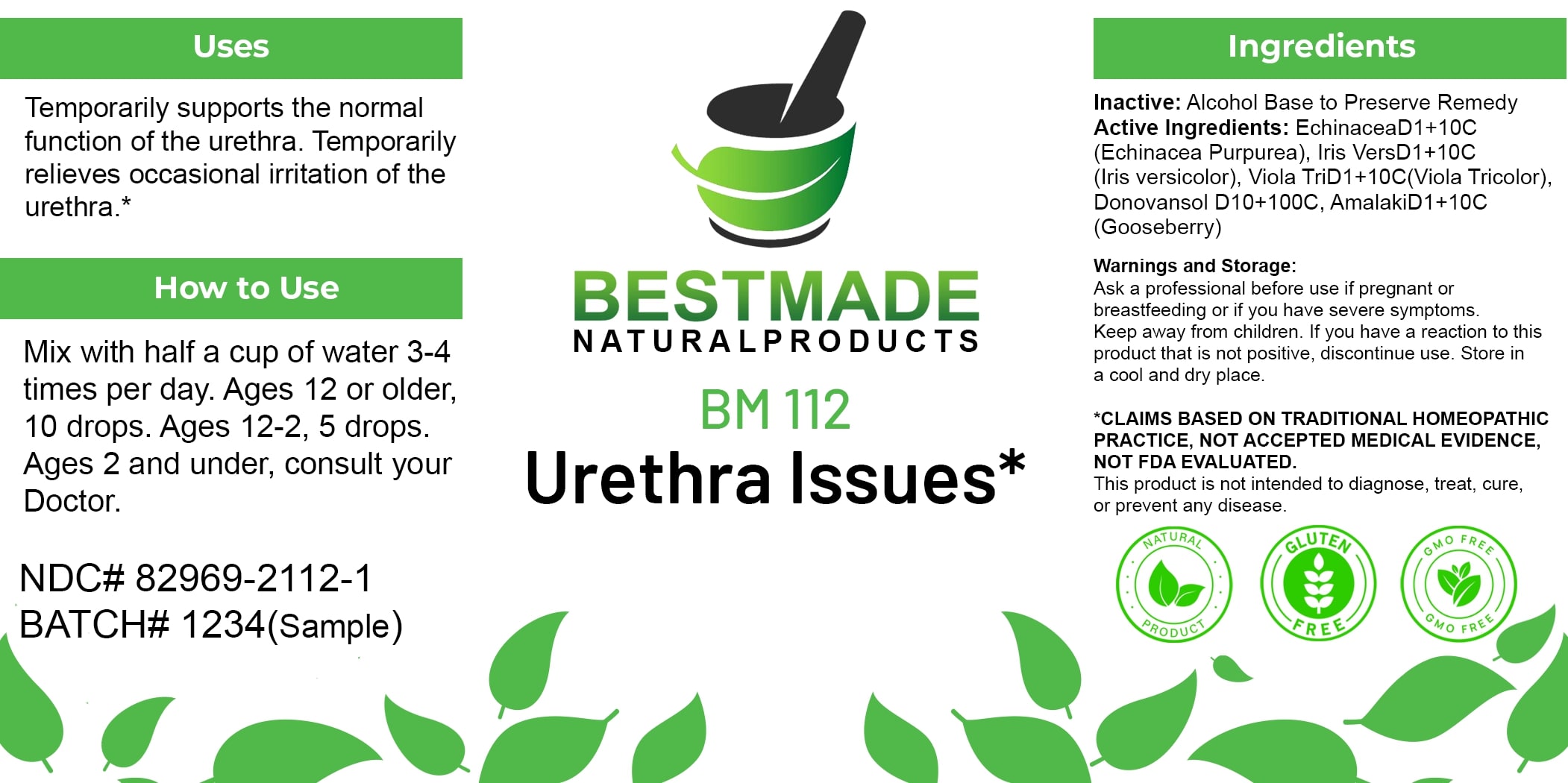 DRUG LABEL: Bestmade Natural Products BM112
NDC: 82969-2112 | Form: LIQUID
Manufacturer: Bestmade Natural Products
Category: homeopathic | Type: HUMAN OTC DRUG LABEL
Date: 20250207

ACTIVE INGREDIENTS: VIOLA TRICOLOR 10 [hp_C]/10 [hp_C]; ARSENIC TRIIODIDE 10 [hp_C]/10 [hp_C]; ECHINACEA, UNSPECIFIED 10 [hp_C]/10 [hp_C]; IRIS VERSICOLOR ROOT 10 [hp_C]/10 [hp_C]; EMBLICA OFFICINALIS FRUIT 10 [hp_C]/10 [hp_C]; MERCURIC IODIDE 10 [hp_C]/10 [hp_C]
INACTIVE INGREDIENTS: ALCOHOL 10 [hp_C]/10 [hp_C]

BM112

DOSAGE AND ADMINISTRATION

How to Use

Mix with half a cup of water 3-4 times per day. Ages 12 or older, 10 drops. Ages 12-2, 5 drops. Ages 2 and under, consult your Doctor.

INACTIVE INGREDIENT

Ingredients

Inactive: Alcohol Base to Preserve Remedy

ACTIVE INGREDIENT

Active Ingredients: EchinaceaD1+10C (Echinacea Purpurea), Iris VersD1+10C (Iris versicolor), Viola TriD1+10C (Viola Tricolor), Donovansol D10+100C, AmalakiD1+10C (Gooseberry)

Uses

Temporarily supports the normal function of the urethra. Temporarily relieves occasional irritation of the urethra.*

*CLAIMS BASED ON TRADITIONAL HOMEOPATHIC PRACTICE, NOT ACCEPTED MEDICAL EVIDENCE, NOT FDA EVALUATED.

This product is not intended to diagnose, treat, cure, or prevent any disease.

Uses

Temporarily supports the normal function of the urethra. Temporarily relieves occasional irritation of the urethra.*

*CLAIMS BASED ON TRADITIONAL HOMEOPATHIC PRACTICE, NOT ACCEPTED MEDICAL EVIDENCE, NOT FDA EVALUATED.

This product is not intended to diagnose, treat, cure, or prevent any disease.

KEEP OUT OF REACH OF CHILDREN

Warnings and Storage:

Ask a professional before use if pregnant or breastfeeding or if you have severe symptoms. Keep away from children. If you have a reaction to this product that is not positive, discontinue use. Store in a cool and dry place.

Warnings and Storage:

Ask a professional before use if pregnant or breastfeeding or if you have severe symptoms. Keep away from children. If you have a reaction to this product that is not positive, discontinue use. Store in a cool and dry place.

*CLAIMS BASED ON TRADITIONAL HOMEOPATHIC PRACTICE, NOT ACCEPTED MEDICAL EVIDENCE, NOT FDA EVALUATED.

This product is not intended to diagnose, treat, cure, or prevent any disease.

Entire package label